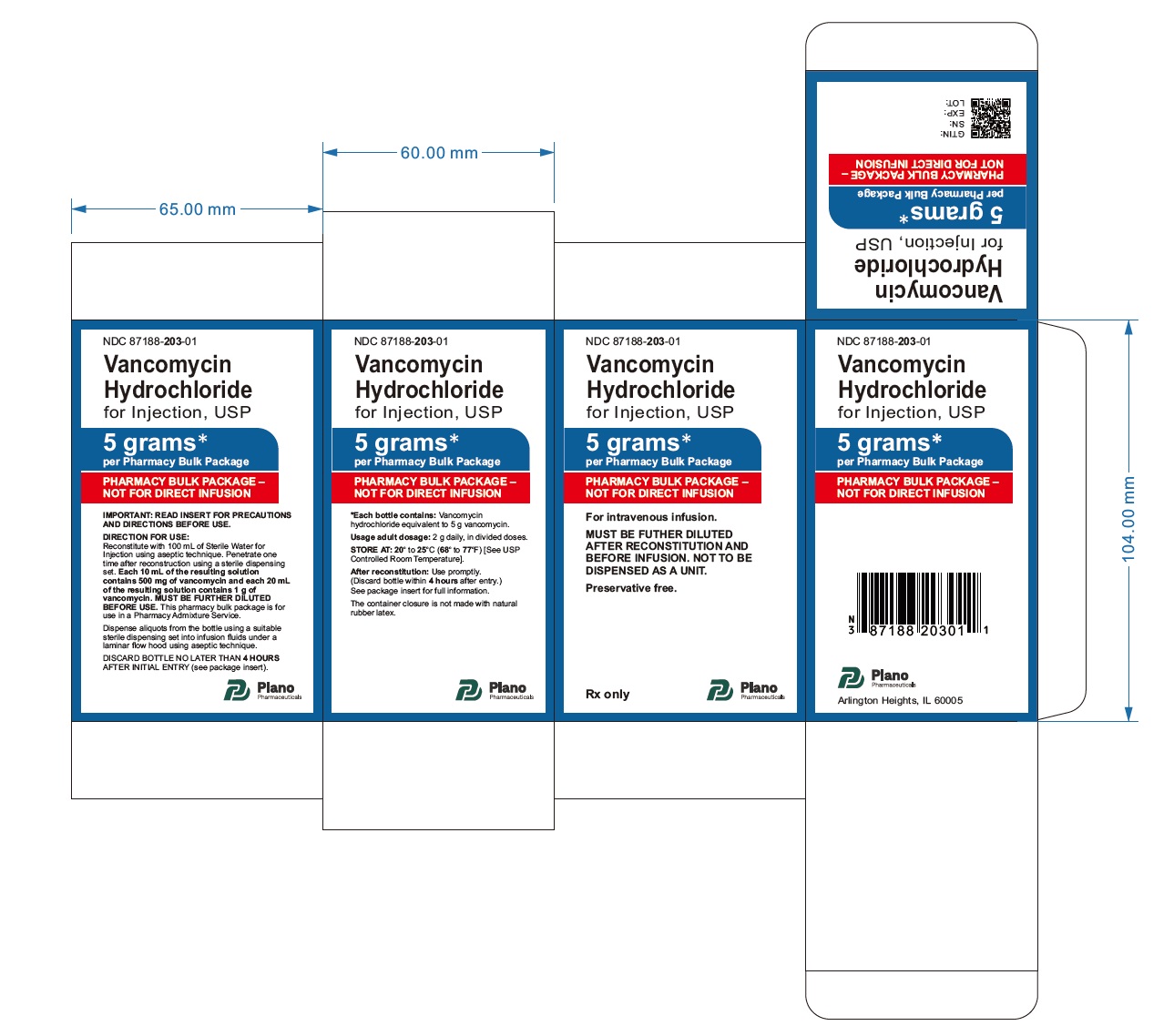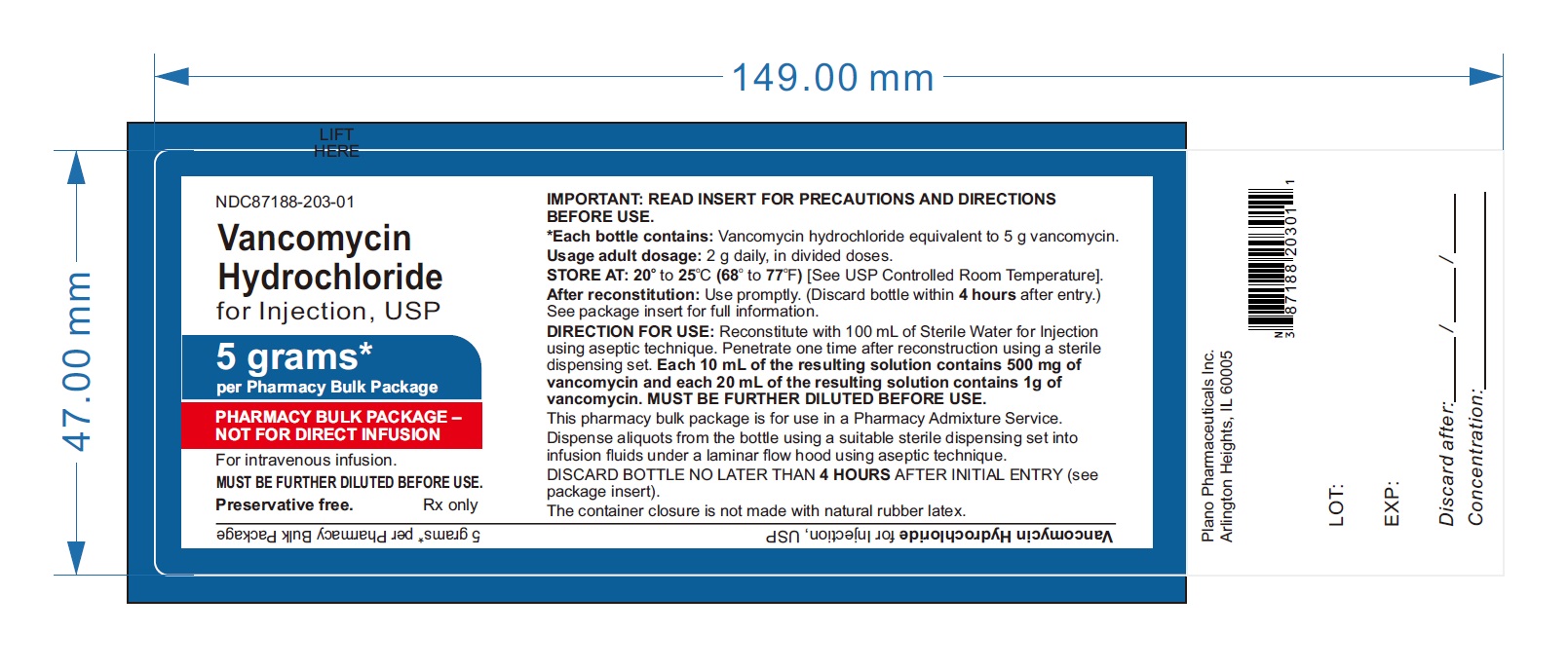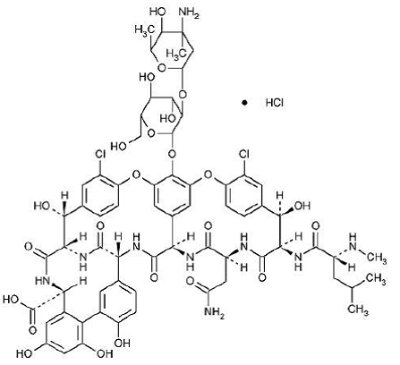 DRUG LABEL: Vancomycin Hydrochloride
NDC: 87188-203 | Form: INJECTION, POWDER, LYOPHILIZED, FOR SOLUTION
Manufacturer: Plano Pharmaceuticals Inc.
Category: prescription | Type: HUMAN PRESCRIPTION DRUG LABEL
Date: 20260224

ACTIVE INGREDIENTS: VANCOMYCIN HYDROCHLORIDE 5 g/100 mL

Vancomycin Hydrochloride, USP

PHARMACY BULK PACKAGE- Not for Direct Infusion

To reduce the development of drug-resistant bacteria and maintain the effectiveness of Vancomycin Hydrochloride for injection, USP and other antibacterial drugs, Vancomycin Hydrochloride for injection, USP should be used only to treat or prevent infections that are proven or strongly suspected to be caused by bacteria.

DESCRIPTION

Sterile Vancomycin Hydrochloride, USP is a lyophilized powder, for preparing intravenous (IV) infusions, in vials containing the equivalent of 5 g or 10 g vancomycin base. 500 mg of the base are equivalent to 0.34 mmol. When reconstituted with Sterile Water for Injection to a concentration of 50 mg/mL for the 5 g vial and 100 mg/mL for the 10 g vial, the pH of the solution is between 2.5 and 4.5. Sterile Vancomycin Hydrochloride, USP should be administered intravenously in diluted solution (see DOSAGE AND ADMINISTRATION).

Sterile Vancomycin Hydrochloride is a tricyclic glycopeptide antibiotic derived from Amyco-latopasis orientalis (formerly Nocardia orientals). The chemical name for vancomycin hydrochloride is 3S-[3R*,6S*(S*),7S*,22S*,23R*,26R*,36S*,38aS*]]-3-(2-Amino-2-oxoethyl)-44-[[2-O-(3-amino-2,3,6-trideoxy-3-C-methyl-α-L-lyxo-hexopyranosyl)-ß-D-glucopyranosyl]oxy]-10,19-dichloro-2,3,4,5,6,7,23,24,25,26,36,37,38,38a-tetradecahydro-7,22,28,30,32-pentahydroxy-6-[[4-methyl-2-(methylamino)-1-oxopentyl]amino]-2,5,24,38,39-pentaoxo-22H-8,11:18,21-dietheno-23,36- (iminomethano)-13,16:31,35-dimetheno-1H,16H- [1,6,9]oxadiazacyclohexadecino[4,5-m][10,2,16]-benzoxadiazacyclotetracosine-26-carboxylic acid, monohydrochloride. The molecular formula is C66H75Cl2N9O24• HCl and the molecular weight is 1,485.74.Vancomycin hydrochloride has the following structural formula:

A pharmacy bulk packageis a sterile dosage form containing many single doses. The contents are intended for use in a pharmacy admixture program and are restricted to the preparation of admixtures for IV infusion.

FURTHER DILUTION IS REQUIRED BEFORE USE.

CLINICAL PHARMACOLOGY

Vancomycin is poorly absorbed after oral administration.

In subjects with normal kidney function, multiple intravenous dosing of 1 g of vancomycin (15 mg/kg) infused over 60 minutes produces mean plasma concentrations of approximately 63 mcg/mL immediately at the completion of infusion, mean plasma concentrations of approximately 23 mcg/mL 2 hours after infusion, and mean plasma concentrations of approximately 8 mcg/mL 11 hours after the end of the infusion. Multiple dosing of 500 mg infused over 30 minutes produces mean plasma concentrations of about 49 mcg/mL at the completion of infusion, mean plasma concentrations of about 19 mcg/mL 2 hours after infusion, and mean plasma concentrations of about 10 mcg/mL 6 hours after infusion. The plasma concentrations during multiple dosing are similar to those after a single dose.

The mean elimination half-life of vancomycin from plasma is 4 to 6 hours in subjects with normal renal function. In the first 24 hours, about 75% of an administered dose of vancomycin is excreted in urine by glomerular filtration. Mean plasma clearance is about 0.058 L/kg/h, and mean renal clearance is about 0.048 L/kg/hr. Renal dysfunction slows excretion of vancomycin. In anephric patients, the average half-life of elimination is 7.5 days. The distribution coefficient is from 0.3 to 0.43 L/kg. There is no apparent metabolism of the drug. About 60% of an intraperitoneal dose of vancomycin administered during peritoneal dialysis is absorbed systemically in 6 hours. Serum concentrations of about 10 mcg/mL are achieved by intraperitoneal injection of 30 mg/kg of vancomycin.

However, the safety and efficacy of the intraperitoneal use of vancomycin has not been established in adequate and well-controlled trials (see PRECAUTIONS).

Total systemic and renal clearance of vancomycin may be reduced in the elderly. Vancomycin is approximately 55% serum protein bound as measured by ultrafiltration at vancomycin serum concentrations of 10 to 100 mcg/mL. After intravenous administration of vancomycin, inhibitory concentrations are present in pleural, pericardial, ascitic, and synovial fluids; in urine; in peritoneal dialysis fluid; and in atrial appendage tissue. Vancomycin does not readily diffuse across normal meninges into the spinal fluid; but, when the meninges are inflamed, penetration into the spinal fluid occurs.

Microbiology

The bactericidal action of vancomycin results primarily from inhibition of cell-wall biosynthesis. In addition, vancomycin alters bacterial-cell-membrane permeability and RNA synthesis. There is no cross-resistance between vancomycin and other antibiotics. Vancomycin is not active in vitroagainst gram-negative bacilli, mycobacteria, or fungi.

Synergy

The combination of vancomycin and an aminoglycoside acts synergistically in vitroagainst many strains of Staphylococcus aureus, Streptococcus bovis,enterococci, and the viridans group streptococci.

Vancomycin has been shown to be active against most strains of the following microorganisms, both in vitroand in clinical infections as described in the INDICATIONS AND USAGEsection.

Aerobic gram-positive microorganisms

Diphtheroids

Enterococci (e.g., Enterococcus faecalis)

Staphylococci, including Staphylococcus aureus and Staphylococcus epidermidis(including heterogeneous methicillin-resistant strains)

Streptococcus bovis

Viridans group streptococci

The following in vitrodata are available, but their clinical significance is unknown.

Vancomycin exhibits in vitroMIC's of 1 mcg/mL or less against most (≥90%) strains of streptococci listed below and MIC's of 4 mcg/mL or less against most (≥90%) strains of other listed microorganisms; however, the safety and effectiveness of vancomycin in treating clinical infections due to these microorganisms have not been established in adequate and well-controlled clinical trials.

Aerobic gram-positive microorganisms

Listeria monocytogenes

Streptococcus pyogenes

Streptococcus pneumoniae(including penicillin-resistant strains)

Streptococcus agalactiae

Anaerobic gram-positive microorganisms

Actinomycesspecies

Lactobacillusspecies

Susceptibility Testing

For specific information regarding susceptibility test interpretive criteria and associated test methods and quality control standards recognized by FDA for this drug, please see: https://www.fda.gov/STIC.

INDICATIONS AND USAGE

Vancomycin Hydrochloride for injection, USP is indicated for the treatment of serious or severe infections caused by susceptible strains of methicillin-resistant (β-lactam-resistant) staphylococci. It is indicated for penicillin-allergic patients, for patients who cannot receive or who have failed to respond to other drugs, including the penicillins or cephalosporins, and for infections caused by vancomycin-susceptible organisms that are resistant to other antimicrobial drugs. Vancomycin Hydrochloride for injection, USP is indicated for initial therapy when methicillin-resistant staphylococci are suspected, but after susceptibility data are available, therapy should be adjusted accordingly.

Vancomycin Hydrochloride for injection, USP is effective in the treatment of staphylococcal endocarditis. Its effectiveness has been documented in other infections due to staphylococci, including septicemia, bone infections, lower respiratory tract infections, skin and skin structure infections. When staphylococcal infections are localized and purulent, antibiotics are used as adjuncts to appropriate surgical measures.

Vancomycin Hydrochloride for injection, USP has been reported to be effective alone or in combination with an aminoglycoside for endocarditis caused by S. viridans or S. bovis. For endocarditis caused by enterococci (e.g., E. faecalis), vancomycin has been reported to be effective only in combination with an aminoglycoside.

Vancomycin Hydrochloride for injection, USP has been reported to be effective for the treatment of diphtheroid endocarditis. Vancomycin Hydrochloride for injection, USP has been used successfully in combination with either rifampin, an aminoglycoside, or both in early-onset prosthetic valve endocarditis caused by S. epidermidis or diphtheroids.

Specimens for bacteriologic cultures should be obtained in order to isolate and identify causative organisms and to determine their susceptibilities to vancomycin.

To reduce the development of drug-resistant bacteria and maintain the effectiveness of Vancomycin Hydrochloride for injection, USP and other antibacterial drugs, Vancomycin Hydrochloride for injection, USP should be used only to treat or prevent infections that are proven or strongly suspected to be caused by susceptible bacteria. When culture and susceptibility information are available, they should be considered in selecting or modifying antibacterial therapy. In the absence of such data, local epidemiology and susceptibility patterns may contribute to the empiric selection of therapy.

The parenteral form of vancomycin hydrochloride may be administered orally for treatment of antibiotic-associated pseudomembranous colitis produced by C. difficile and for staphylococcal enterocolitis. Parenteral administration of vancomycin hydrochloride alone is of unproven benefit for these indications. Vancomycin is not effective by the oral route for other types of infections.

CONTRAINDICATIONS

Vancomycin hydrochloride for injection is contraindicated in patients with known hypersensitivity to this antibiotic.

WARNINGS

Infusion Reactions

Rapid bolus administration (e.g., over several minutes) may be associated with exaggerated hypotension, including shock and rarely cardiac arrest.

Vancomycin hydrochloride for injection should be administered in a diluted solution over a period of not less than 60 minutes to avoid rapid-infusion-related reactions. Stopping the infusion usually results in prompt cessation of these reactions.

Nephrotoxicity

Systemic vancomycin exposure may result in acute kidney injury (AKI). The risk of AKI increases as systemic exposure/serum levels increase. Monitor renal function in all patients, especially patients with underlying renal impairment, patients with co-morbidities that predispose to renal impairment, and patients receiving concomitant therapy with a drug known to be nephrotoxic.

Ototoxicity

Ototoxicity has occurred in patients receiving vancomycin hydrochloride for injection. It may be transient or permanent. It has been reported mostly in patients who have been given excessive doses, who have an underlying hearing loss, or who are receiving concomitant therapy with another ototoxic agent, such as an aminoglycoside. Vancomycin should be used with caution in patients with renal insufficiency because the risk of toxicity is appreciably increased by high, prolonged blood concentrations.

Dosage of vancomycin hydrochloride for injection must be adjusted for patients with renal dysfunction (see PRECAUTIONS and DOSAGE AND ADMINISTRATION).

Severe dermatologic reactions such as toxic epidermal necrolysis (TEN), Stevens-Johnson syndrome (SJS), drug reaction with eosinophilia and systemic symptoms (DRESS), acute generalized exanthematous pustulosis (AGEP), and linear IgA bullous dermatosis (LABD) have been reported in association with the use of vancomycin. Cutaneous signs or symptoms reported include skin rashes, mucosal lesions, and blisters.

Discontinue vancomycin hydrochloride for injection at the first appearance of signs and symptoms of TEN, SJS, DRESS, AGEP, or LABD.

Clostridium difficile associated diarrhea (CDAD) has been reported with use of nearly all antibacterial agents, including vancomycin hydrochloride for injection, and may range in severity from mild diarrhea to fatal colitis. Treatment with antibacterial agents alters the normal flora of the colon leading to overgrowth of C. difficile.

C. difficile produces toxins A and B which contribute to the development of CDAD. Hypertoxin producing strains of C. difficile cause increased morbidity and mortality, as these infections can be refractory to antimicrobial therapy and may require colectomy. CDAD must be considered in all patients who present with diarrhea following antibiotic use. Careful medical history is necessary since CDAD has been reported to occur over two months after the administration of antibacterial agents.

If CDAD is suspected or confirmed, ongoing antibiotic use not directed against C. difficile may need to be discontinued. Appropriate fluid and electrolyte management, protein supplementation, antibiotic treatment of C. difficile, and surgical evaluation should be instituted as clinically indicated.

Hemorrhagic Occlusive Retinal Vasculitis (HORV)

Hemorrhagic occlusive retinal vasculitis, including permanent loss of vision, occurred in patients receiving intracameral or intravitreal administration of vancomycin during or after cataract surgery. The safety and efficacy of vancomycin administered by the intracameral or the intravitreal route have not been established by adequate and well-controlled trials. Vancomycin is not indicated for the prophylaxis of endophthalmitis.

PRECAUTIONS

Clinically significant serum concentrations have been reported in some patients being treated for active C. difficile-induced pseudomembranous colitis after multiple oral doses of vancomycin.

Prolonged use of vancomycin hydrochloride for injection may result in the overgrowth of nonsusceptible microorganisms. Careful observation of the patient is essential. If superinfection occurs during therapy, appropriate measures should be taken. In rare instances, there have been reports of pseudomembranous colitis due to C. difficile developing in patients who received intravenous vancomycin hydrochloride for injection.

Serial tests of auditory function may be helpful in order to minimize the risk of ototoxicity.

Reversible neutropenia has been reported in patients receiving vancomycin hydrochloride for injection (see ADVERSE REACTIONS). Patients who will undergo prolonged therapy with vancomycin hydrochloride for injection or those who are receiving concomitant drugs which may cause neutropenia should have periodic monitoring of the leukocyte count.

Vancomycin hydrochloride for injection is irritating to tissue and must be given by a secure intravenous route of administration. Pain, tenderness, and necrosis occur with intramuscular (IM) injection of vancomycin hydrochloride for injection or with inadvertent extravasation. Thrombophlebitis may occur, the frequency and severity of which can be minimized by administering the drug slowly as a dilute solution (2.5 to 5 g/L) and by rotation of venous access sites.

There have been reports that the frequency of infusion-related events (including hypotension, flushing, erythema, urticaria, and pruritus) increases with the concomitant administration of anesthetic agents. Infusion-related events may be minimized by the administration of vancomycin as a 60-minute infusion prior to anesthetic induction. The safety and efficacy of vancomycin administered by the intrathecal (intralumbar or intraventricular) route or by the intraperitoneal route have not been established by adequate and well controlled trials.

Reports have revealed that administration of sterile vancomycin by the intraperitoneal route during continuous ambulatory peritoneal dialysis (CAPD) has resulted in a syndrome of chemical peritonitis. To date, this syndrome has ranged from cloudy dialysate alone to a cloudy dialysate accompanied by variable degrees of abdominal pain and fever. This syndrome appears to be short-lived after discontinuation of intraperitoneal vancomycin.

Prescribing vancomycin hydrochloride for injection in the absence of a proven or strongly suspected bacterial infection or a prophylactic indication is unlikely to provide benefit to the patient and increases the risk of the development of drug-resistant bacteria.

Drug Interactions

Concomitant administration of vancomycin and anesthetic agents has been associated with erythema and histamine-like flushing (see Pediatric Use - PRECAUTIONS) and anaphylactoid reactions (see ADVERSE REACTIONS).

Monitor renal function in patients receiving vancomycin and concurrent and/or sequential systemic or topical use of other potentially, neurotoxic and/or nephrotoxic drugs, such as amphotericin B, aminoglycosides, bacitracin, polymixin B, colistin, viomycin, or cisplatin.

Carcinogenesis, Mutagenesis, Impairment of Fertility

Although no long-term studies in animals have been performed to evaluate carcinogenic potential, no mutagenic potential of Sterile Vancomycin Hydrochloride was found in standard laboratory tests. No definitive fertility studies have been performed.

Pregnancy

Teratogenic Effects

Animal reproduction studies have not been conducted with vancomycin. It is not known whether vancomycin can affect reproduction capacity. In a controlled clinical study, the potential ototoxic and nephrotoxic effects of vancomycin on infants were evaluated when the drug was administered to pregnant women for serious staphylococcal infections complicating intravenous drug abuse. Vancomycin was found in cord blood. No sensorineural hearing loss or nephrotoxicity attributable to vancomycin was noted. One infant whose mother received vancomycin in the third trimester experienced conductive hearing loss that was not attributed to the administration of vancomycin. Because the number of patients treated in this study was limited and vancomycin was administered only in the second and third trimesters, it is not known whether vancomycin causes fetal harm. Vancomycin should be given to a pregnant woman only if clearly needed.

Nursing Mothers

Vancomycin hydrochloride for injection is excreted in human milk. Caution should be exercised when vancomycin hydrochloride for injection is administered to a nursing woman. Because of the potential for adverse events, a decision should be made whether to discontinue nursing or to discontinue the drug, taking into account the importance of the drug to the mother.

Pediatric Use

In premature neonates and young infants, it may be appropriate to confirm desired vancomycin serum concentrations. Concomitant administration of vancomycin and anesthetic agents has been associated with erythema and histamine-like flushing in pediatric patients (see ADVERSE REACTIONS).

Geriatrics

The natural decrement of glomerular filtration with increasing age may lead to elevated vancomycin serum concentrations if dosage is not adjusted. Vancomycin dosage schedules should be adjusted in elderly patients (see DOSAGE AND ADMINISTRATION).

Information for Patients

Advise patients about the signs and symptoms of serious skin manifestations. Instruct patients to stop vancomycin hydrochloride for injection immediately and promptly seek medical attention at the first signs or symptoms of skin rash, mucosal lesions and blisters (see WARNINGS).

Patients should be counseled that antibacterial drugs including vancomycin hydrochloride for injection should only be used to treat bacterial infections. They do not treat viral infections (e.g., the common cold). When vancomycin hydrochloride for injection is prescribed to treat a bacterial infection, patients should be told that although it is common to feel better early in the course of therapy, the medication should be taken exactly as directed. Skipping doses or not completing the full course of therapy may (1) decrease the effectiveness of the immediate treatment and (2) increase the likelihood that bacteria will develop resistance and will not be treatable by vancomycin hydrochloride for injection or other antibacterial drugs in the future.

Diarrhea is a common problem caused by antibiotics which usually ends when the antibiotic is discontinued. Sometimes after starting treatment with antibiotics, patients can develop watery and bloody stools (with or without stomach cramps and fever) even as late as two or more months after having taken the last dose of the antibiotic. If this occurs, patients should contact their physician as soon as possible.

ADVERSE REACTIONS

To report SUSPECTED ADVERSE REACTIONS, contact Plano Pharmaceuticals Inc. at 1-773-726-1154 or FDA at 1-800-FDA-1088 or www.fda.gov/medwatch.

Infusion-Related Events

During or soon after rapid infusion of Sterile Vancomycin Hydrochloride, patients may develop anaphylactoid reactions, including hypotension (see ANIMAL PHARMACOLOGY), wheezing, dyspnea, urticaria, or pruritus. Rapid infusion may also cause flushing of the upper body ("red neck") or pain and muscle spasm of the chest and back. These reactions usually resolve within 20 minutes but may persist for several hours. Such events are infrequent if Sterile Vancomycin Hydrochloride is given by a slow infusion over 60 minutes. In studies of normal volunteers, infusion-related events did not occur when Sterile Vancomycin Hydrochloride was administered at a rate of 10 mg/min or less.

Nephrotoxicity

Systemic vancomycin exposure may result in acute kidney injury (AKI). The risk of AKI increases as systemic exposure/serum levels increase. Additional risk factors for AKI in patients receiving vancomycin include receipt of concomitant drugs known to be nephrotoxic, in patients with pre-exiting renal impairment, or with co-morbidities that predispose to renal impairment. Interstitial nephritis has also been reported in patients receiving vancomycin.

Gastrointestinal

Onset of pseudomembranous colitis symptoms may occur during or after antibiotic treatment (see WARNINGS).

Ototoxicity

A few dozen cases of hearing loss associated with Sterile Vancomycin Hydrochloride have been reported. Most of these patients had kidney dysfunction or a preexisting hearing loss or were receiving concomitant treatment with an ototoxic drug. Vertigo, dizziness, and tinnitus have been reported rarely.

Hematopoietic

Reversible neutropenia, usually starting 1 week or more after onset of therapy with vancomycin or after a total dosage of more than 25 g, has been reported for several dozen patients.

Neutropenia appears to be promptly reversible when vancomycin is discontinued. Thrombocytopenia has rarely been reported. Although a causal relationship has not been established, reversible agranulocytosis (granulocytes <500/mm3) has been reported rarely.

Phlebitis

Inflammation at the injection site has been reported.

Miscellaneous

Patients have been reported to have had anaphylaxis, drug fever, nausea, chills, eosinophilia, rashes including exfoliative dermatitis, Stevens-Johnson syndrome (see WARNINGS, Severe Dermatologic Reactions), and vasculitis in association with the administration of vancomycin.

Chemical peritonitis has been reported following intraperitoneal administration (see PRECAUTIONS)

Post Marketing Reports

The following adverse reactions have been identified during post-approval use of vancomycin. Because these reactions are reported voluntarily from a population of uncertain size, it is not possible to reliably estimate their frequency or establish a causal relationship to drug exposure.

Skin and Subcutaneous Tissue Disorders

Severe dermatologic reactions such as toxic epidermal necrolysis (TEN), drug reaction with eosinophilia and systemic symptoms (DRESS), acute generalized exanthematous pustulosis (AGEP), and linear IgA bullous dermatosis (LABD) (see WARNINGS, Severe Dermatologic Reactions).

OVERDOSAGE

The intent of the pharmacy bulk package for this product is for preparation of solutions for intravenous infusion only.

Supportive care is advised, with maintenance of glomerular filtration. Vancomycin is poorly removed by dialysis. Hemofiltration and hemoperfusion with polysulfone resin have been reported to result in increased vancomycin clearance. The median lethal intravenous dose is 319 mg/kg in rats and 400 mg/kg in mice.

To obtain up-to-date information about the treatment of overdose, a good resource is your certified Regional Poison Control Center. Telephone numbers of certified poison control centers are listed in the Physicians’ Desk Reference (PDR). In managing overdosage, consider the possibility of multiple drug overdoses, interaction among drugs, and unusual drug kinetics in your patient.

DOSAGE AND ADMINISTRATION

Infusion-related events are related to both the concentration and the rate of administration of vancomycin. Concentrations of no more than 5 mg/mL and rates of no more than 10 mg/min, are recommended in adults (see also age-specific recommendations). In selected patients in need of fluid restriction, a concentration up to 10 mg/mL may be used; use of such higher concentrations may increase the risk of infusion-related events. An infusion rate of 10 mg/min or less is associated with fewer infusion-related events (see ADVERSE REACTIONS). Infusion-related events may occur, however, at any rate or concentration.

Patients With Normal Renal Function

Adults

The usual daily intravenous dose is 2 g divided either as 500 mg every 6 hours or 1 g every 12 hours. Each dose should be administered at no more than 10 mg/min or over a period of at least 60 minutes, whichever is longer. Other patient factors, such as age or obesity, may call for modification of the usual intravenous daily dose.

Pediatric patients

The usual intravenous dosage of vancomycin is 10 mg/kg per dose given every 6 hours. Each dose should be administered over a period of at least 60 minutes. Close monitoring of serum concentrations of vancomycin may be warranted in these patients.

Neonates

In pediatric patients up to the age of 1 month, the total daily intravenous dosage may be lower. In neonates, an initial dose of 15 mg/kg is suggested, followed by 10 mg/kg every 12 hours for neonates in the 1st week of life and every 8 hours thereafter up to the age of 1 month. Each dose should be administered over 60 minutes. In premature infants, vancomycin clearance decreases as postconceptional age decreases. Therefore, longer dosing intervals may be necessary in premature infants. Close monitoring of serum concentrations of vancomycin is recommended in these patients.

Patients With Impaired Renal Function and Elderly Patients

Dosage adjustment must be made in patients with impaired renal function. In premature infants and the elderly, greater dosage reductions than expected may be necessary because of decreased renal function. Measurement of vancomycin serum concentrations can be helpful in optimizing therapy, especially in seriously ill patients with changing renal function. Vancomycin serum concentrations can be determined by use of microbiologic assay, radioimmunoassay, fluorescence polarization immunoassay, fluorescence immunoassay, or high-pressure liquid chromatography. If creatinine clearance can be measured or estimated accurately, the dosage for most patients with renal impairment can be calculated using the following table. The dosage of vancomycin hydrochloride for injection per day in mg is about 15 times the glomerular filtration rate in mL/min (see following table).

DOSAGE TABLE FOR VANCOMYCIN IN PATIENTS WITH IMPAIRED RENAL FUNCTION
(Adapted from Moellering et al.^1)
Creatinine Clearance; mL/min | Vancomycin Dose; mg/24 h
100 | 1,545
90 | 1,390
80 | 1,235
70 | 1,080
60 | 925
50 | 770
40 | 620
30 | 465
20 | 310
10 | 155

The initial dose should be no less than 15 mg/kg, even in patients with mild to moderate renal insufficiency. The table is not valid for functionally anephric patients. For such patients, an initial dose of 15 mg/kg of body weight should be given to achieve prompt therapeutic serum concentrations. The dose required to maintain stable concentrations is 1.9 mg/kg/24 hr. In patients with marked renal impairment, it may be more convenient to give maintenance doses of 250 to 1,000 mg once every several days rather than administering the drug on a daily basis. In anuria, a dose of 1,000 mg every 7 to 10 days has been recommended. When only serum creatinine is known, the following formula (based on sex, weight and age of the patient) may be used to calculate creatinine clearance. Calculated creatinine clearances (mL/min) are only estimates. The creatinine clearance should be measured promptly.

Men: | [Weight (kg) x (140 - age in years)]; 72 x serum creatinine concentration (mg/dL)
Women: | 0.85 x above value

The serum creatinine must represent a steady state of renal function. Otherwise, the estimated value for creatinine clearance is not valid. Such a calculated clearance is an overestimate of actual clearance in patients with conditions: (1) characterized by decreasing renal function, such as shock, severe heart failure, or oliguria; (2) in which a normal relationship between muscle mass and total body weight is not present, such as in obese patients or those with liver disease, edema, or ascites; and (3) accompanied by debilitation, malnutrition, or inactivity. The safety and efficacy of vancomycin administration by the intrathecal (intralumbar or intraventricular) routes have not been established. Intermittent infusion is the recommended method of administration.

Compatibility with Other Drugs and IV Fluids

The following diluents are physically and chemically compatible (with 4 g/L vancomycin hydrochloride):

5% Dextrose Injection, USP

5% Dextrose Injection and 0.9% Sodium Chloride Injection, USP

Lactated Ringer’s Injection, USP

5% Dextrose and Lactated Ringer’s Injection

Normosol ® -M and 5% Dextrose

0.9% Sodium Chloride Injection, USP

Isolyte ® E

Good professional practice suggests that compounded admixtures should be administered as soon after preparation as is feasible.

Vancomycin solution has a low pH and may cause physical instability of other compounds.

Preparation and Stability

For Administration by Intravenous Drip

Refer to Directions for Proper Use of a Pharmacy Bulk Package Bottle.

DIRECTIONS FOR PROPER USE OF PHARMACY BULK PACKAGE

a.The container closure may be penetrated only one time after reconstitution, utilizing a suitable sterile dispensing set which allows measured distribution of the contents.
b.Use of this product is restricted to a suitable work area, such as a laminar flow hood.
c.Once this container closure has been punctured, withdrawal of the contents should be completed without delay. If prompt fluid transfer cannot be accomplished, discard the contents no later than 4 HOURS after initial closure puncture. This time limit should begin with the introduction of solvent for diluent into the Pharmacy Bulk Package.

Parenteral drug products should be visually inspected for particulate matter and discoloration prior to administration, whenever solution and container permit.

Do not add supplementary medication to Vancomycin for Injection, USP.

Preparation and Stability

5 g Pharmacy Bulk Package bottle

At the time of use, reconstitute by adding 100 mL of Sterile Water for Injection to the 5 g Pharmacy Bulk Package bottle of dry, sterile vancomycin powder. The resultant solution will contain vancomycin equivalent to 500 mg/10 mL. FURTHER DILUTION IS REQUIRED.

Reconstituted solutions of vancomycin (500 mg/10 mL) must be further diluted in at least 100 mL of a suitable infusion solution. Doses of 1 gram/20 mL must be further diluted in at least 200 mL of a suitable infusion solution. The desired dose diluted in this manner should be administered by intermittent intravenous infusion over a period of at least 60 minutes.

10 g Pharmacy Bulk Package bottle

At the time of use, reconstitute by adding 95 mL of Sterile Water for Injection, USP to the 10 g bottle of dry, sterile vancomycin powder. The resultant solution will contain vancomycin equivalent to 500 mg/5 mL (1 g/10 mL). AFTER RECONSTITUTION, FURTHER DILUTION IS REQUIRED.

Reconstituted solutions of vancomycin (500 mg/5 mL) must be further diluted in at least 100 mL of a suitable infusion solution. For doses of 1 gram (10 mL), at least 200 mL of solution must be used. The desired dose diluted in this manner should be administered by intermittent intravenous infusion over a period of at least 60 minutes.

Parenteral drug products should be visually inspected for particulate matter and discoloration prior to administration, whenever solution and container permit.

For Oral Administration

Oral vancomycin is used in treating antibiotic-associated pseudomembranous colitis caused by C. difficile and for staphylococcal enterocolitis. Vancomycin is not effective by the oral route for other types of infections. The usual adult total daily dosage is 500 mg to 2 g given in 3 or 4 divided doses for 7 to 10 days. The total daily dose in children is 40 mg/kg of body weight in 3 or 4 divided doses for 7 to 10 days. The total daily dosage should not exceed 2 g. The appropriate dose may be diluted in 1 oz of water and given to the patients to drink. Common flavoring syrups may be added to the solution to improve the taste for oral administration. The diluted solution may be administered via a nasogastric tube.

HOW SUPPLIED

Vancomycin Hydrochloride for Injection, USP, supplied as follows:

Unit of Sale | Strength
NDC 87188-203-01; Individually; Packaged | Vancomycin hydrochloride; equivalent to 5 grams; vancomycin in a Pharmacy; Bulk Package Bottle
NDC 87188-204-01; Individually; Packaged | Vancomycin hydrochloride; equivalent to 10 grams; vancomycin in a Pharmacy; Bulk Package Bottle

Store at 20° to 25°C (68° to 77°F) [see USP Controlled Room Temperature].

The container closure is not made with natural rubber latex.

ANIMAL PHARMACOLOGY

In animal studies, hypotension and bradycardia occurred in dogs receiving an intravenous infusion of vancomycin hydrochloride 25 mg/kg, at a concentration of 25 mg/mL and an infusion rate of 13.3 mL/min.

REFERENCES

1.Moellering RC, Krogstad DJ, Greenblatt DJ: Vancomycin therapy in patients with impaired renal function: A nomogram for dosage. Ann Inter Med 1981;94:343.

Revised: Apirl, 2026

Distributed by Plano Pharmaceuticals Inc.

125 S Wilke Rd. suite 353, Arlington Heights, IL 60005

DOSAGE AND ADMINISTRATION

Infusion-related events are related to both the concentration and the rate of administration of vancomycin. Concentrations of no more than 5 mg/mL and rates of no more than 10 mg/min, are recommended in adults (see also age-specific recommendations). In selected patients in need of fluid restriction, a concentration up to 10 mg/mL may be used; use of such higher concentrations may increase the risk of infusion-related events. An infusion rate of 10 mg/min or less is associated with fewer infusion-related events (see ADVERSE REACTIONS). Infusion-related events may occur, however, at any rate or concentration.

PACKAGE LABEL

NDC 87188-203-01

Vancomycin

Hydrochloride

for Injection, USP

5 grams*

per Pharmacy Bulk Package

PHARMACY BULK PACKAGE – NOT FOR DIRECT INFUSION

For intravenous infusion.

MUST BE FURTHER DILUTED BEFORE USE.

Preservative free. Rx only

IMPORTANT: READ INSERT FOR PRECAUTIONS AND DIRECTIONS BEFORE USE.

*Each bottle contains: Vancomycin hydrochloride equivalent to 5 g vancomycin.

Usage adult dosage: 2 g daily, in divided doses.

STORE AT: 20o to 25oC (68o to 77oF) [See USP Controlled Room Temperature].

After reconstitution: Use promptly. (Discard bottle within 4 hours after entry.) See package insert for full information.

DIRECTION FOR USE: Reconstitute with 100 mL of Sterile Water for Injection using aseptic technique. Penetrate one time after reconstruction using a sterile dispensing set. Each 10 mL of the resulting solution contains 500 mg of vancomycin and each 20 mL of the resulting solution contains 1g of vancomycin. MUST BE FURTHER DILUTED BEFORE USE. This pharmacy bulk package is for use in a Pharmacy Admixture Service.

Dispense aliquots from the bottle using a suitable sterile dispensing set into infusion fluids under a laminar flow hood using aseptic technique.

DISCARD BOTTLE NO LATER THAN 4 HOURS AFTER INITIAL ENTRY (see package insert).

The container closure is not made with natural rubber latex.

Plano Pharmaceuticals Inc.

Arlington Heights, IL 60005

NDC87188-203-01

Vancomycin

Hydrochloride

for Injection, USP

5 grams*

per Pharmacy Bulk Package

PHARMACY BULK PACKAGE – NOT FOR DIRECT INFUSION

Arlington Heights, IL 60005

NDC87188-203-01

Vancomycin

Hydrochloride

for Injection, USP

5 grams*

per Pharmacy Bulk Package

PHARMACY BULK PACKAGE – NOT FOR DIRECT INFUSION

*Each bottle contains: Vancomycin hydrochloride equivalent to 5 g vancomycin.

Usage adult dosage: 2 g daily, in divided doses.

STORE AT: 20o to 25oC (68o to 77oF) [See USP Controlled Room Temperature].

After Reconstitution: Use promptly. (Discard bottle within 4 hours after entry.) See package insert for full information.

The container closure is not made with natural rubber latex.

NDC 87188-203-01

Vancomycin

Hydrochloride

for Injection, USP

5 grams*

per Pharmacy Bulk Package

PHARMACY BULK PACKAGE – NOT FOR DIRECT INFUSION

For intravenous infusion.

MUST BE FUTHER DILUTED AFTER RECONSTITUTION AND BEFORE INFUSION. NOT TO BE DISPENSED AS A UNIT.

Preservative free.

Rx only

NDC 87188-203-01

Vancomycin

Hydrochloride

for Injection, USP

5 grams*

per Pharmacy Bulk Package

PHARMACY BULK PACKAGE – NOT FOR DIRECT INFUSION

IMPORTANT: READ INSERT FOR PRECAUTIONS AND DIRECTIONS BEFORE USE.

DIRECTION FOR USE:

Reconstitute with 100 mL of Sterile Water for Injection using aseptic technique. Penetrate one time after reconstruction using a sterile dispensing set. Each 10 mL of the resulting solution contains 500 mg of vancomycin and each 20 mL of the resulting solution contains 1g of vancomycin. MUST BE FURTHER DILUTED BEFORE USE. This pharmacy bulk package is for use in a Pharmacy Admixture Service.

Dispense aliquots from the bottle using a suitable sterile dispensing set into infusion fluids under a laminar flow hood using aseptic technique.

DISCARD BOTTLE NO LATER THAN 4 HOURS AFTER INITIAL ENTRY (see package insert)